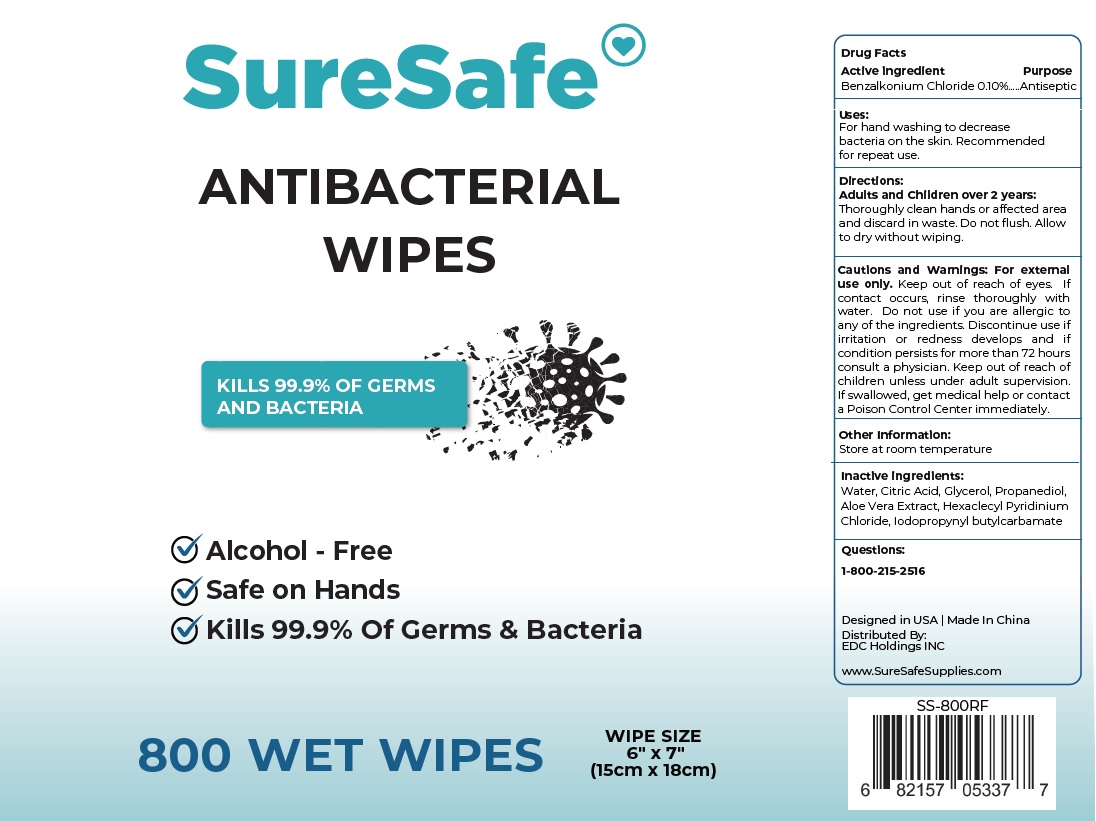 DRUG LABEL: SureSafe ANTIBACTERIAL WIPES
NDC: 80671-003 | Form: CLOTH
Manufacturer: QUANZHOU AIWINA HYGIENE PRODUCTS CO.,LTD
Category: otc | Type: HUMAN OTC DRUG LABEL
Date: 20210212

ACTIVE INGREDIENTS: BENZALKONIUM CHLORIDE 0.1 g/100 mL
INACTIVE INGREDIENTS: WATER; CITRIC ACID MONOHYDRATE; GLYCERIN; PROPANEDIOL; ALOE VERA LEAF; CETYLPYRIDINIUM CHLORIDE ANHYDROUS; IODOPROPYNYL BUTYLCARBAMATE

SureSafe ANTIBACTERIAL WIPES

Active ingredient

Benzalkonium Chloride 0.10%

Purpose

Antiseptic

Uses:

For hand washing to decrease bacteria on the skin. Recommended for repeat use.

Directions:

Adults and Children over 2 years:
Thoroughly clean hands or affected area and discard in waste. Do not flush. Allow to dry without wiping.

Cautions and Warnings:

For external use only. Keep out of reach of eyes. If contact occurs, rinse thoroughly with water. Do not use if you are allergic to any of the ingredients. Discontinue use if irritation or redness develops and if condition persists for more than 72 hours consult a physician.

Keep out of reach of children unless under adult supervision. If swallowed, get medical help or contact a Poison Control Center immediately.

Other Information:

Store at room temperature

Inactive ingredients:

Water, Citric Acid, Glycerol, Propanediol, Aloe Vera Extract, Hexadecyl Pyridinium Chloride, Iodopropynyl butylcarbamate

Questions:

1-800-215-2516

KILLS 99.9% OF GERMS AND BACTERIA

√ Alcohol - Free

√ Safe on Hands

Designed in USA | Made In China

Distributed By:

EDC Holdings INC

www.SureSafeSupplies.com